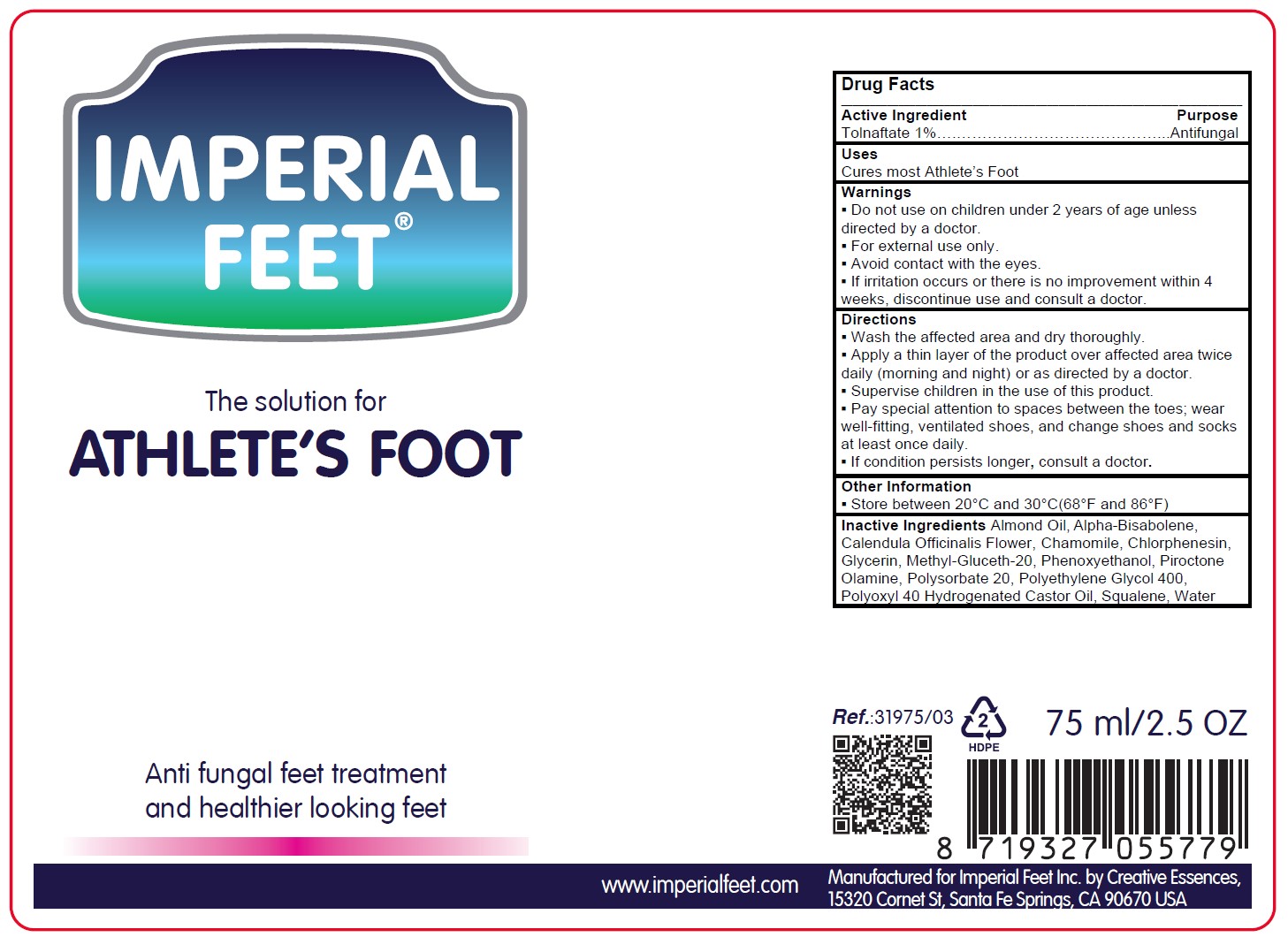 DRUG LABEL: Athletes Foot
NDC: 83837-002 | Form: SOLUTION/ DROPS
Manufacturer: Imperial Feet B.V.
Category: otc | Type: HUMAN OTC DRUG LABEL
Date: 20251021

ACTIVE INGREDIENTS: TOLNAFTATE 1 g/100 mL
INACTIVE INGREDIENTS: CALENDULA OFFICINALIS FLOWER; CHLORPHENESIN; GLYCERIN; PIROCTONE OLAMINE; ALMOND OIL; POLYOXYL 40 HYDROGENATED CASTOR OIL; WATER; SQUALENE; METHYL GLUCETH-20; .ALPHA.-BISABOLOL, (+)-; PHENOXYETHANOL; POLYSORBATE 20; CHAMOMILE FLOWER OIL; POLYETHYLENE GLYCOL 400

Athlete's Foot 75 mL NDC 83837-002-01

Active Ingredient

Tolnaftate 1%

Warnings

. Do not use on children under 2 years of age unless directed by a doctor.
. For external use only.
. Avoid contact with the eyes.
. If irritation occurs or there is no improvement within 4 weeks, discontinue use and consult a doctor.

Ask a doctor

If irritation occurs or there is no improvement within 4 weeks, discontinue use and consult a doctor.

Stop Use

If irritation occurs or there is no improvement within 4 weeks, discontinue use and consult a doctor.

Inactive Ingredient

Inactive Ingredients Almond Oil, Alpha-Bisabolene,
Calendula Officinalis Flower, Chamomile, Chlorphenesin,
Glycerin, Methyl-Gluceth-20, Phenoxyethanol, Piroctone
Olamine, Polysorbate 20, Polyethylene Glycol 400,
Polyoxyl 40 Hydrogenated Castor Oil, Squalene, Water

Other Information

Store between 20 C and 30 C (68 F and 86 F)

Purpose

Antifungal

Directions

- Wash the affected area and dry thoroughly.
- Apply a thin layer of the product over affected area twice daily (morning and night) or as directed by a doctor.
- Supervise children in the use of this product.
- Pay special attention to spaces between the toes; wear well-fitting, ventilated shoes, and change shoes and socks at least once daily.
- If condition persists longer, consult a doctor.

Keep out of reach of children

Supervise children in the use of this product

Use

Cures most Athlete's Foot